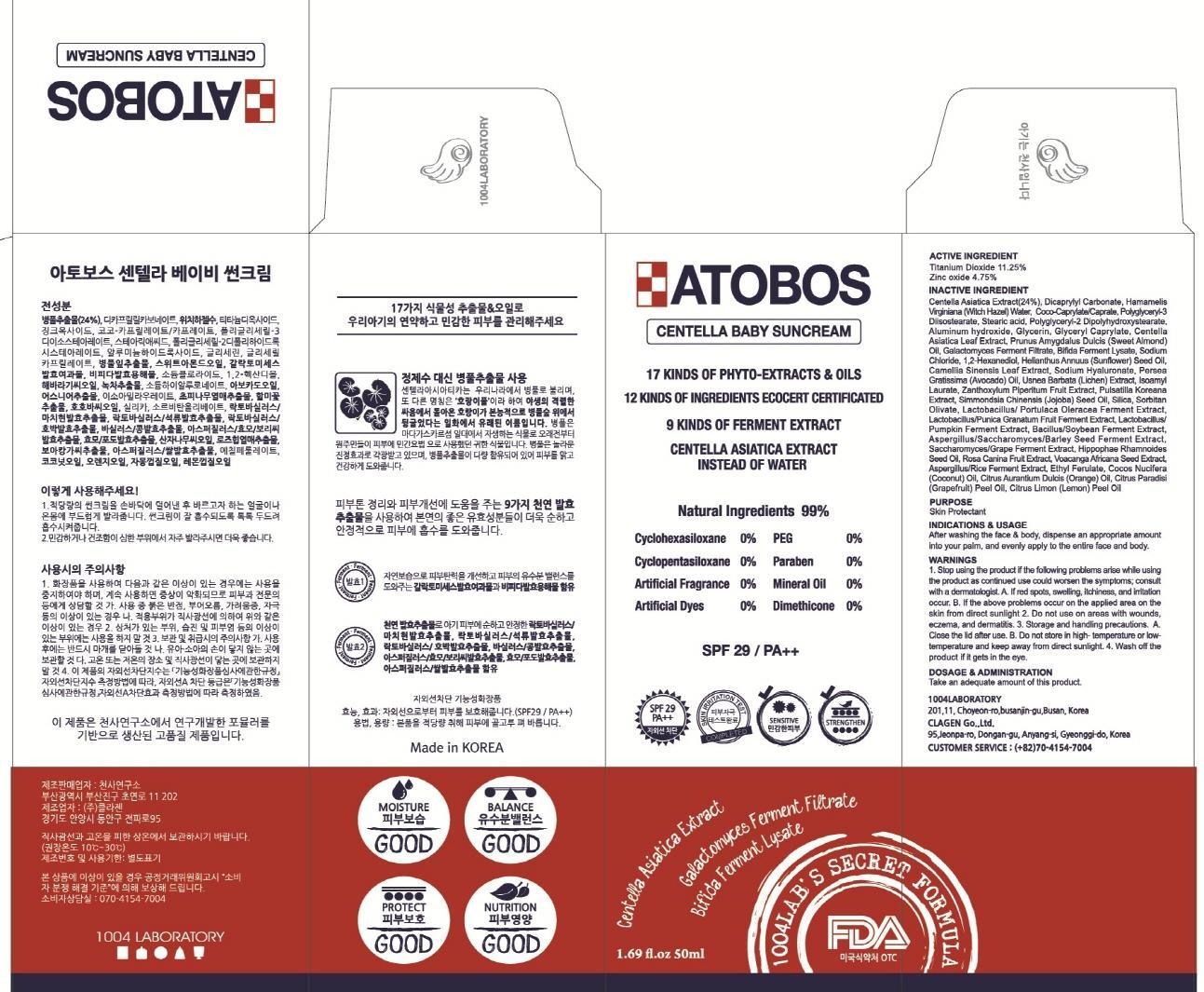 DRUG LABEL: ATOBOS CENTELLA BABY SUN
NDC: 69739-120 | Form: CREAM
Manufacturer: 1004LABORATORY
Category: otc | Type: HUMAN OTC DRUG LABEL
Date: 20150831

ACTIVE INGREDIENTS: Titanium Dioxide 5.62 mg/50 mL; Zinc oxide 2.37 mg/50 mL
INACTIVE INGREDIENTS: Centella Asiatica; Dicaprylyl Carbonate

ACTIVE INGREDIENT

Active Ingredient: Titanium Dioxide 11.25% , Zinc oxide 4.75%

INACTIVE INGREDIENT

Inactive Ingredients: Centella Asiatica Extract(24%), Dicaprylyl Carbonate, Hamamelis Virginiana (Witch Hazel) Water, Coco-Caprylate/Caprate, Polyglyceryl-3 Diisostearate, Stearic acid, Polyglyceryl-2 Dipolyhydroxystearate, Aluminum hydroxide, Glycerin, Glyceryl Caprylate, Centella Asiatica Leaf Extract, Prunus Amygdalus Dulcis (Sweet Almond) Oil, Galactomyces Ferment Filtrate, Bifida Ferment Lysate, Sodium Chloride, 1,2-Hexanediol, Helianthus Annuus (Sunflower) Seed Oil, Camellia Sinensis Leaf Extract, Sodium Hyaluronate, Persea Gratissima (Avocado) Oil, Usnea Barbata (Lichen) Extract, Isoamyl Laurate, Zanthoxylum Piperitum Fruit Extract, Pulsatilla Koreana Extract, Simmondsia Chinensis (Jojoba) Seed Oil, Silica, Sorbitan Olivate, Lactobacillus/Portulaca Oleracea Ferment Extract, Lactobacillus/Punica Granatum Fruit Ferment Extract, Lactobacillus/Pumpkin Ferment Extract, Bacillus/Soybean Ferment Extract, Aspergillus/Saccharomyces/ Barley Seed Ferment Extract, Saccharomyces/Grape Ferment Extract, Hippophae Rhamnoides Seed Oil, Rosa Canina Fruit Extract, Voacanga Africana Seed Extract, Aspergillus/Rice Ferment Extract, Ethyl Ferulate, Cocos Nucifera (Coconut) Oil, Citrus Aurantium Dulcis (Orange) Oil, Citrus Paradisi (Grapefruit) Peel Oil, Citrus Limon (Lemon) Peel Oil

PURPOSE

Purpose: Sunscreen

WARNINGS

Warnings: 1. Stop using the product if the following problems arise while using the product as continued use could worsen the symptoms; consult with a dermatologist. A. If red spots, swelling, itchiness, and irritation occur. B. If the above problems occur on the applied area on the skin from direct sunlight 2. Do not use on areas with wounds, eczema, and dermatitis. 3. Storage and handling precautions. A. Close the lid after use. B. Do not store in high- temperature or low- temperature and keep away from direct sunlight.

DESCRIPTION

Indications & Usage: After washing the face & body, dispense an appropriate amount into your palm, and evenly apply to the entire face and body.

Dosage & Administration: Take an adequate amount of this product.